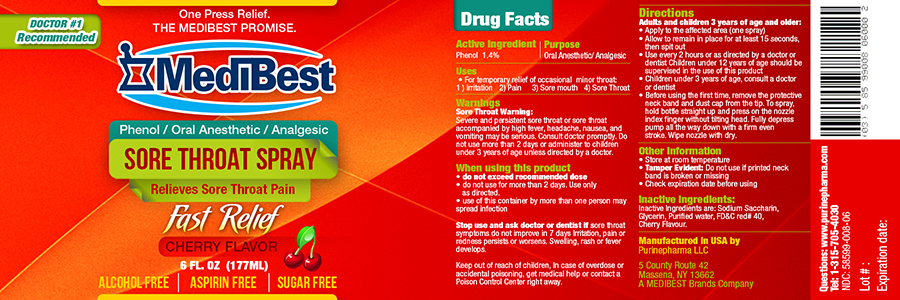 DRUG LABEL: Phenol
NDC: 58599-008 | Form: SPRAY
Manufacturer: PURINEPHARMA LLC
Category: otc | Type: HUMAN OTC DRUG LABEL
Date: 20150615

ACTIVE INGREDIENTS: PHENOL 1.4 mg/1 mL
INACTIVE INGREDIENTS: SACCHARIN SODIUM; GLYCERIN; WATER; FD&C RED NO. 40; CHERRY

SORE THROAT SPRAY

Active Ingredient:
Phenol 1.4%

Purpose: Oral Anesthetic/ Analgesic

Uses

- For the temporary relief of occasional minor throat:
  1. Irritation
  2. Pain
  3. Sore Mouth
  4. Sore Throat

Warnings

Sore Throat Warnings:
Severe and persisttent sore throat or sore throat accompanied by high fever, headache, nausea, and vomiting may be serious. Consult doctor promptly. Do not use more than 2 days or administer to children under 3 years of age unless directed by a doctor.

- do not exceed recommended dose
- do not use for more than 2 days. Use only aas directed.
- use of this container by more than one person may spread infection.

Stop use and ask doctor or dentist if sore throat symptoms do not improve in 7 days Irritation, pain or redness persists or worsens. Swelling, rash or fever develops.

WHEN USING

- do not exceed recommended dose
- do not use for more than 2 days. Use only aas directed.
- use of this container by more than one person may spread infection.

Keep out of reach of children. In case of overdose or accidental poisioning, get medical help or contact a Poison Control Center right away.

Directions

Adults and children 3 years of age and older:

- Apply to the affected area (one spray)
- Allow to remain in place for at least 15 seconds, then spit out
- Use every 2 hours or as directed by a doctor or dentist. Children under 12 years of age should be supervised in the use of this product
- Children under 3 years of age, consult a doctor or dentist
- Before using the first time, remove the protective neck band and dust cap from the tip. To spray, hold bottle straight up and press on the nozzle with index finger without tiltting head. Fully depress pump all the way down with a firm even stroke. Wipe nizzle dry.

Other information

- Store at room temperature
- Temper Evident: Do not use if printed neck band is broken or missing
- Check expiration date before using

INACTIVE INGREDIENT

Inactive ingredients are: Sodium Saccharin, Glycerin, Purified water, FD&C red# 40, Cherry Flavour.

HOW SUPPLIED

Manufactured in USA by
Purinepharma LLC
5 County Route 42
Massena, NY 13662
A MEDIBEST Brands Company
Questions: www.purinepharma.com
Tel: 1-315-705-4030
NDC: 58599-008-06